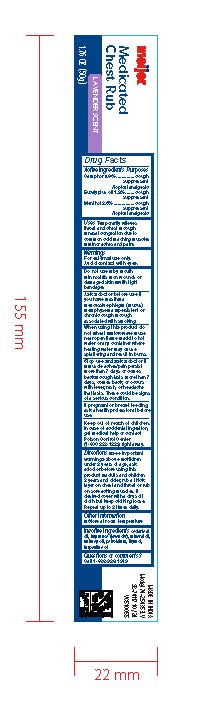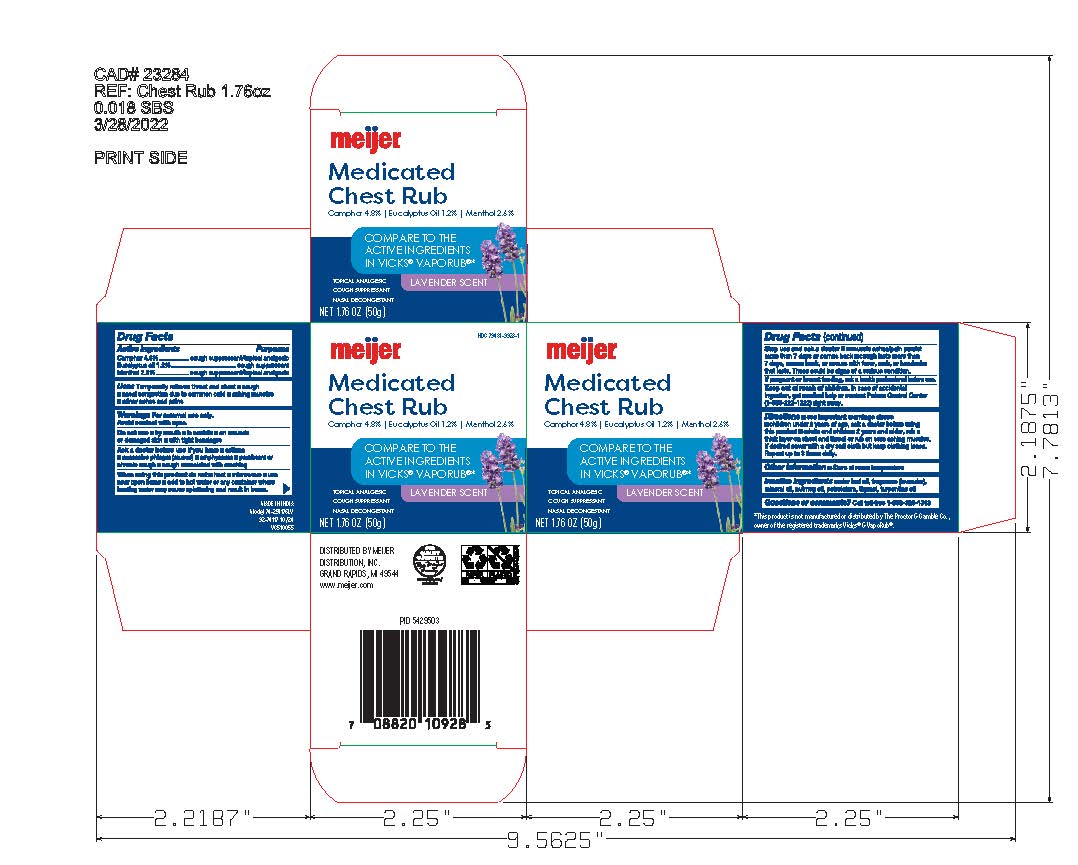 DRUG LABEL: Meijer Medicated Chest Rub, 3.53 oz. Lavender
NDC: 79481-9928 | Form: GEL
Manufacturer: Meijer Distribution
Category: otc | Type: HUMAN OTC DRUG LABEL
Date: 20241203

ACTIVE INGREDIENTS: CAMPHOR (SYNTHETIC) 4.8 g/100 g; EUCALYPTUS OIL 1.2 g/100 g; MENTHOL 2.6 g/100 g
INACTIVE INGREDIENTS: TURPENTINE OIL; PETROLATUM; MINERAL OIL; NUTMEG OIL; CEDAR LEAF OIL; THYMOL

Meijer Medicated Chest Rub, 1.76 oz. Lavender

Active Ingredients

Camphor 4.8%

Eucalyptus oil 1.2%

Menthol 2.6%

Purpose

Cough suppressant/topical analgesic

Uses

Uses Temporarily relieves throat and chest ■cough ■ nasal congestion due to common cold ■aching muscles ■ minor aches and pains

Warnings

For external use only

Avoid contact with eyes

Do not use ■by mouth ■ in nostrils ■on wounds
or damaged skin ■ with tight bandages

Ask a doctor before use if you have ■asthma ■excessive phlegm (mucus) ■emphysema ■persistent or chronic cough ■cough associated with smoking

When using this product do not

■heat ■microwave ■use near open flame ■ Add hot water or any container where heating water may cause splattering and result in burns.

Stop Use and ask a doctor if

■muscle aches/pain persists more than 7 days()(comes back ■cough lasts more than 7 days, comes back, or occurs with fever, rash, or headache that lasts. These could be signs of a serious condition.

If pregnant or breast feeding

ask a health professional before use

Keep out of reach of children

. In case of accidental ingestion, get medical help, or contact Poison Control Center (1-800-222-1222) right away

Directions

■ see important warnings above ■children under 2 years of age, ask a doctor before using this product ■adults and children 2 years and older, rub a thick layer on chest and throat or rub on sore aching muscles. If desired cover it with a dry soft cloth but keep clothing loose. Repeat up to 3 times daily.

Inactive Ingredients

cedar leaf oil, fragrance (lavender), mineral oil, nutmeg oil, petrolatum, thymol, turpentine oil

Questions or comments

Call toll free 1-866-326-1313